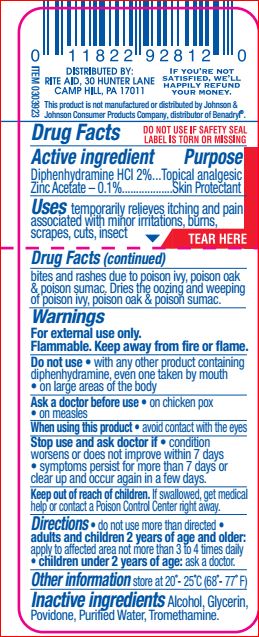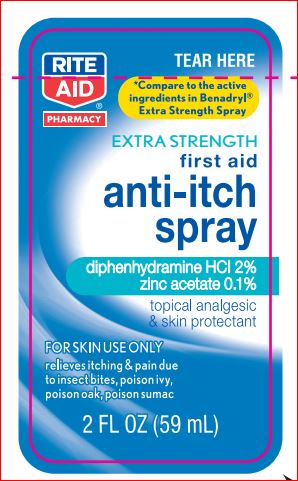 DRUG LABEL: Extra Strength First Aid Anti-itch
NDC: 11822-7796 | Form: SPRAY
Manufacturer: Rite Aid
Category: otc | Type: HUMAN OTC DRUG LABEL
Date: 20180518

ACTIVE INGREDIENTS: DIPHENHYDRAMINE HYDROCHLORIDE 2 g/100 mL; ZINC ACETATE ANHYDROUS 0.1 g/100 mL
INACTIVE INGREDIENTS: Alcohol; Glycerin; Povidone; Water; Tromethamine

Drug Facts

Active ingredients Purpose

Diphenhydramine HCl – 2% Topical analgesic
Zinc Acetate – 0.1% Skin Protectant

Uses

temporarily relieves itching and pain associated with minor irritations, burns, scrapes, cuts, insect bites and rashes due to poison oak & poison sumac. Dries the oozing and weeping of poison ivy, poison oak & poison sumac.

Warnings For external use only. Flammable. Keep away from fire or flame.

Do not use • with any other product containing Diphenhydramine, even onetaken by mouth • on large areas of the body

Ask a doctor before use

• on chicken pox

• on measles

When using this product • avoid contact with eyes

Stop use and ask a doctor if
• condition worsens or does not improve within 7 days
• symptoms persist more than 7 days or clear up and occur again within a few days

Keep out of reach of the children
If product is swallowed, get medical help or contact a Poison Control Center right away

Directions

• do not use more than directed • adults and children 2 years of age and older: apply to affected area not more than 3 to 4 times daily • children under 2 years of age: ask a doctor

Other information

Store at 20o - 25oC (68o - 77oF)

Inactive ingredients

Alcohol, Glycerin, Povidone, Purified Water, Tromethamine